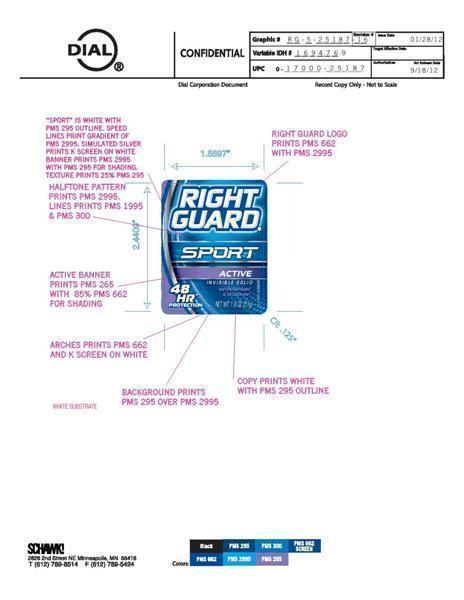 DRUG LABEL: Right Guard Sport
NDC: 51815-208 | Form: STICK
Manufacturer: VVF Illinois Services LLC
Category: otc | Type: HUMAN OTC DRUG LABEL
Date: 20130528

ACTIVE INGREDIENTS: ALUMINUM ZIRCONIUM TRICHLOROHYDREX GLY 7.14 g/51 g
INACTIVE INGREDIENTS: CYCLOMETHICONE; STEARYL ALCOHOL; PPG-14 BUTYL ETHER; HYDROGENATED CASTOR OIL; TALC; CETYL ALCOHOL; MYRISTYL MYRISTATE; POLYETHYLENE GLYCOL 500

Right Guard Sport Active

Active ingredient

Aluminum Zirconium Trichlorohydrex GLY 16.0%

Use

- Reduces underarm perspiration

WARNINGS

For External use only

Do not use on broken skin

Stop use and ask doctor if rash or irritation occurs

Keep out of reach of children. If swallowed, get medical help or contact a poison control center right away

Ask a doctor before use if you have kidney disease

Directions

Apply to underarms only

Inactive ingredients

cyclomethicone, stearyl alcohol, PPG-14 butyl ether,

hydrogenated castor oil, talc, cetyl alcohol, myristyl

myristate, fragrance, polyethylene.

Questions

Questions? 1 800-258-DIAL

Directions

Apply to underarms only